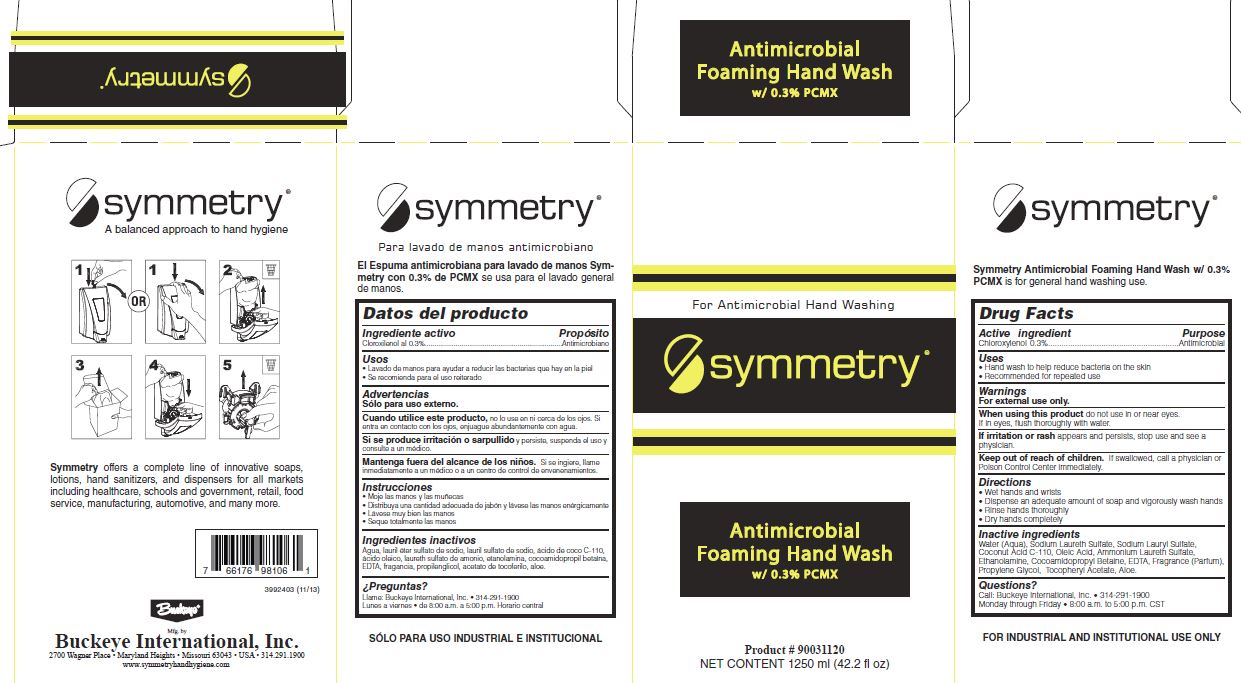 DRUG LABEL: Symmetry Antimicrobial Foaming Hand Wash
NDC: 30805-006 | Form: SOLUTION
Manufacturer: Buckeye International, Inc.
Category: otc | Type: HUMAN OTC DRUG LABEL
Date: 20241115

ACTIVE INGREDIENTS: CHLOROXYLENOL 0.3 g/100 mL
INACTIVE INGREDIENTS: WATER; SODIUM LAURETH SULFATE; SODIUM LAURYL SULFATE; COCONUT ACID; OLEIC ACID; MONOETHANOLAMINE; COCAMIDOPROPYL BETAINE; EDETIC ACID; PROPYLENE GLYCOL; .ALPHA.-TOCOPHEROL ACETATE; ALOE; AMMONIUM LAURETH-3 SULFATE

Drug Facts 30805-006

Active ingredient

Chloroxylenol 0.3%

Purpose

Antimicrobial

Uses

Hand wash to help reduce bacteria on the skin

Recommended for repeated use

Warnings

For external use only.

When using this product do not use in or near eyes.

If in eyes, flush thoroughly with water.

ADVERSE REACTIONS

If irritation or rash appears and persists, stop use and see a physician.

Keep out of reach of children.

If swallowed, call a physician or Poison Control Center immediately.

Directions

Wet hands and wrists

Dispense an adequate amount of soap and vigorously wash hands

Rinse hands thoroughly

Dry hands completely

Inactive ingredients

Water (Aqua), Sodium Laureth Sulfate, Sodium Lauryl Sulfate, Coconut Acid C-110, Oleic Acid, Ammonium Laureth Sulfate, Ethanolamine, Cocoamidopropyl Betaine, EDTA,

Fragrance (Parfum), Propylene Glycol, Tocopheyl Acetate, Aloe.

Questions?

Call: Buckeye International, Inc.

314-291-1900

Monday through Friday

8:00 a.m. to 5:00p.m. CST

PACKAGE LABEL

For Antimicrobial Hand Washing

Symmetry

Antimicrobial

Foaming Hand Wash

with 0.3% PCMX

Product 90031120

Net Contents 1250 ml (42.2 fl oz)